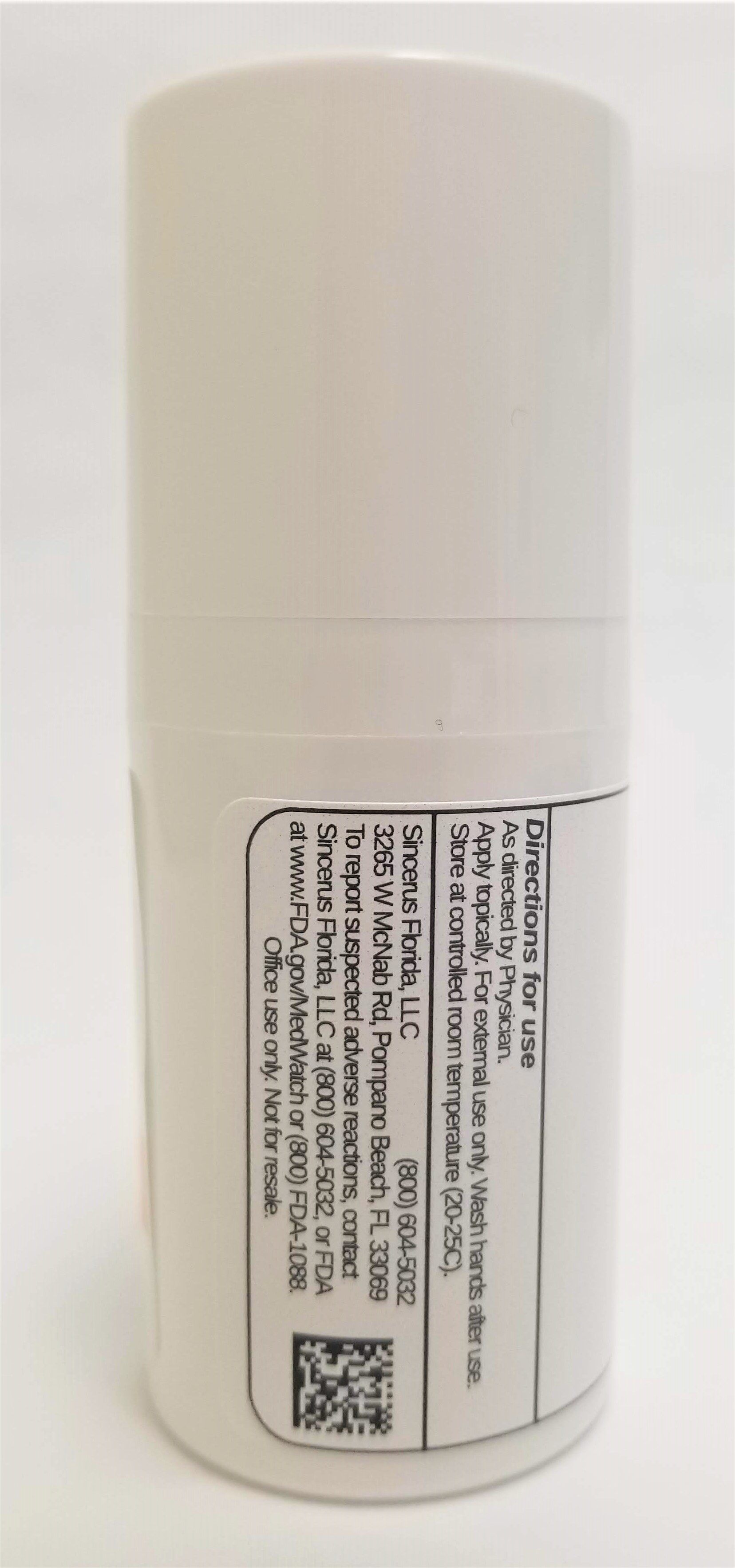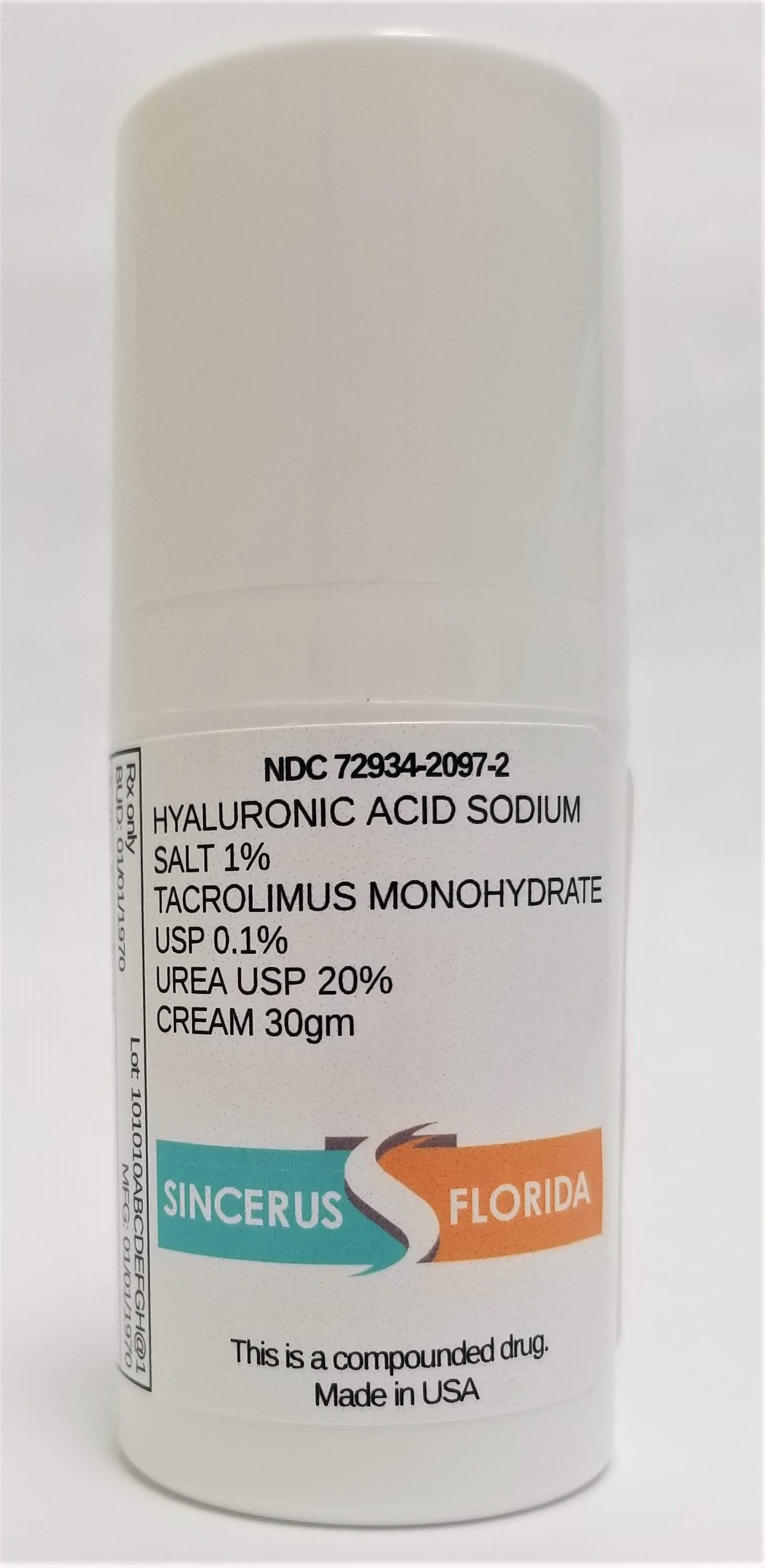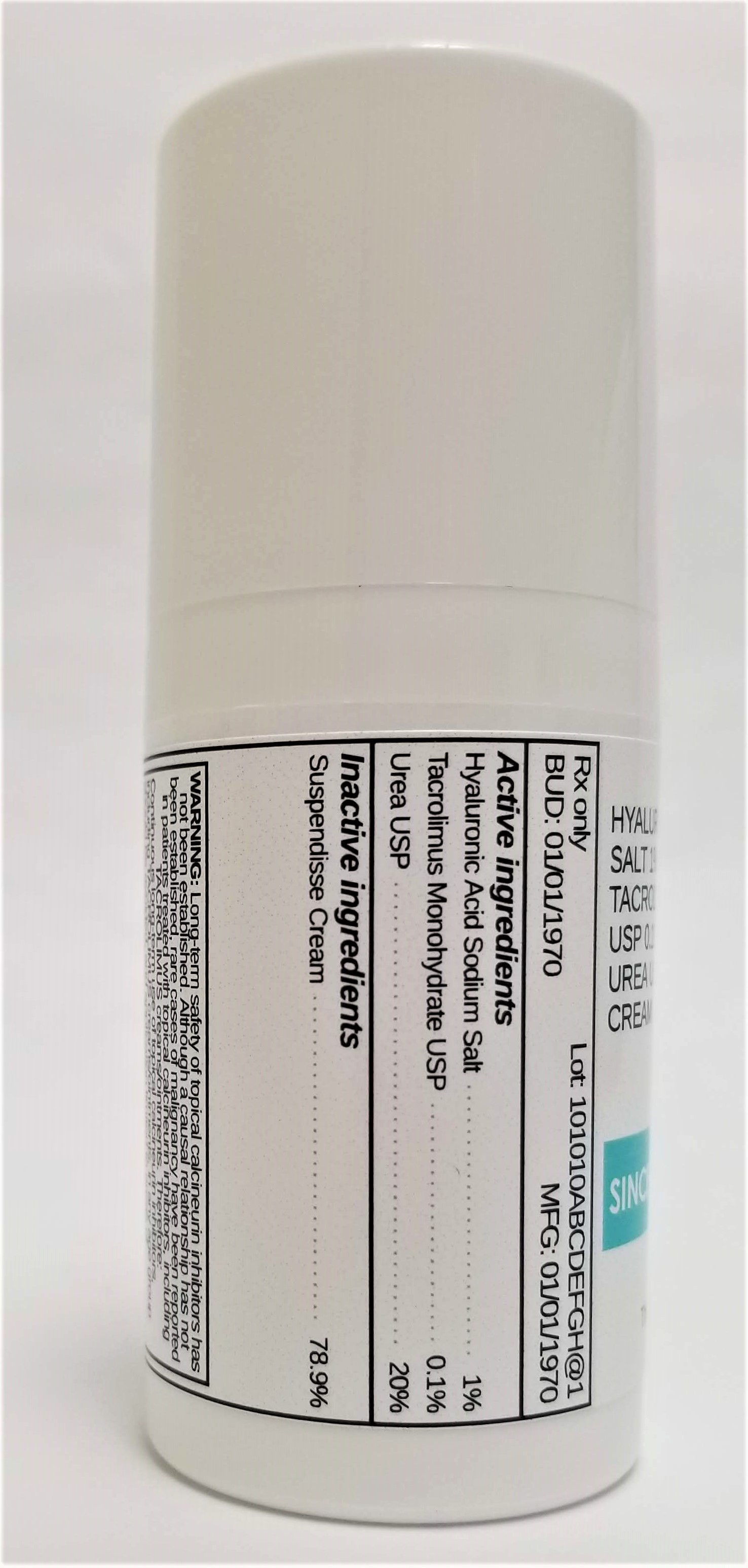 DRUG LABEL: HYALURONIC ACID SODIUM SALT 1% / TACROLIMUS 0.1% / UREA 20%
NDC: 72934-2097 | Form: CREAM
Manufacturer: Sincerus Florida, LLC
Category: prescription | Type: HUMAN PRESCRIPTION DRUG LABEL
Date: 20190516

ACTIVE INGREDIENTS: UREA 20 g/100 g; HYALURONATE SODIUM 1 g/100 g; TACROLIMUS 0.1 g/100 g

HYALURONIC ACID SODIUM SALT 1% / TACROLIMUS 0.1% / UREA 20%